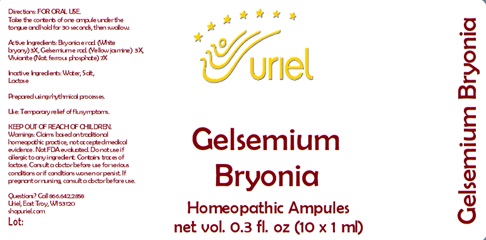 DRUG LABEL: Gelsemium Bryonia
NDC: 48951-5004 | Form: LIQUID
Manufacturer: Uriel Pharmacy Inc.
Category: homeopathic | Type: HUMAN OTC DRUG LABEL
Date: 20241220

ACTIVE INGREDIENTS: BRYONIA ALBA ROOT 3 [hp_X]/1 mL; GELSEMIUM SEMPERVIRENS ROOT 3 [hp_X]/1 mL; FERROSOFERRIC PHOSPHATE 7 [hp_X]/1 mL
INACTIVE INGREDIENTS: WATER; SODIUM CHLORIDE; LACTOSE

Gelsemium Bryonia

INDICATIONS AND USAGE

Directions: FOR ORAL USE.

DOSAGE AND ADMINISTRATION

Take the contents of one ampule under the tongue and hold for 30 seconds, then swallow.

Active Ingredients: Bryonia e rad. (White
bryony) 3X, Gelsemium e rad. (Yellow jasmine) 3X, Vivianite (Nat. ferrous phosphate) 7X

Inactive Ingredients: Water, Salt, Lactose

Prepared using rhythmical processes.

PURPOSE

Use: Temporary relief of flu symptoms.

KEEP OUT OF REACH OF CHILDREN.

WARNINGS

Warnings: Claims based on traditional homeopathic practice, not accepted medical evidence. Not FDA evaluated. Do not use if allergic to any ingredient. Contains traces of lactose. Consult a doctor before use for serious conditions or if conditions worsen or persist. If pregnant or nursing, consult a doctor before use.

Questions? Call 866.642.2858
Uriel, East Troy, WI 53120
shopuriel.com Lot: